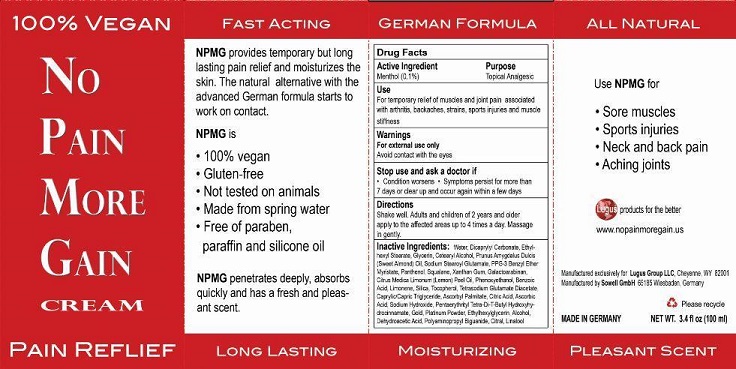 DRUG LABEL: No Pain More Gain
NDC: 71618-001 | Form: CREAM
Manufacturer: Compes Cosmetic
Category: otc | Type: HUMAN OTC DRUG LABEL
Date: 20181216

ACTIVE INGREDIENTS: MENTHOL 10 mg/100 mg
INACTIVE INGREDIENTS: WATER; DICAPRYLYL CARBONATE; ETHYLHEXYL STEARATE; GLYCERIN; CETOSTEARYL ALCOHOL; ALMOND OIL; SODIUM STEAROYL GLUTAMATE; PPG-3 BENZYL ETHER MYRISTATE; PANTHENOL; SQUALANE; XANTHAN GUM; GALACTOARABINAN; LEMON OIL; PHENOXYETHANOL; BENZOIC ACID; LIMONENE, (+)-; SILICON DIOXIDE; TOCOPHEROL; TETRASODIUM GLUTAMATE DIACETATE; CAPRYLIC/CAPRIC/LAURIC TRIGLYCERIDE; ASCORBYL PALMITATE; CITRIC ACID MONOHYDRATE; ASCORBIC ACID; SODIUM HYDROXIDE; PENTAERYTHRITOL TETRAKIS(3-(3,5-DI-TERT-BUTYL-4-HYDROXYPHENYL)PROPIONATE); GOLD; PLATINUM; ETHYLHEXYLGLYCERIN; ALCOHOL; DEHYDROACETIC ACID; POLYAMINOPROPYL BIGUANIDE; CITRAL; LINALOOL, (+)-

Active Ingredient Purpose

Menthol (0.1%) Topical Analgesic

Use

For temporary relief of muscles and joint pain associated with arthritis, backaches, strains, sports injuries and muscle stiffness

Keep out of reach of children.

Directions

Shake Well. Adults and children of 2 years and older apply to the affected areas up to 4 times a day. Massage in gently.

Warnings

For external use only

Avoid contact with the eyes

Stop use and ask a doctor if

- Condition worsens
- Symptoms persist for more than 7 days or clear up and occur again within a few days

INDICATIONS AND USAGE

100% Vegan

No Pain More Gain Cream

Moisturizing Pain Relief

NPMG provides temporary but long lasting pain relief and moisturizes the skin. The natural alternative with the advanced German formula starts to work on contact.

NPMG is

100% vegan

gluten-free

not tested on animals

made from spring water

free of paraben, paraffin and silicone oil

NPMG penetrates deeply, absorbs quickly and has a fresh and pleasant scent.

Lugus products for the better.

Manufactured exclusively for

Lugus Group LLC, Cheyenne, WY 82001

Manufactured by

Sowell GmbH 65185 Wiesbaden, Germany

MADE IN GERMANY

NET WT 3.4 fl oz (100 ml)

Inactive Ingredients

water, dicaprylyl carbonate, ethylhexyl stearate, glycerin, cetearyl alcohol, prunus amygdalis dulcis (sweet almond) oil, sodium stearoyl glutamate, PPG-3 benzyl ether myristate, panthenol, squalane, xanthan gum, galactoarabinan, citrus medica limonum (lemon) peel oil, phenoxyethanol, benzoic acid, limonene, silica, tocopherol, tetrasodium glutamate diacetate, caprylic/capric triglyceride, ascorbyl palmitate, citric acid, ascorbic acid, sodium hydroxide, penthaerythrityl tetra-di-t-butyl hydroxyhydrocinnamate, gold, platinum powder, ethylhexylglycerin, alcohol, dehydroacetic acid, polyaminopropyl biguanide, citral, linalool.